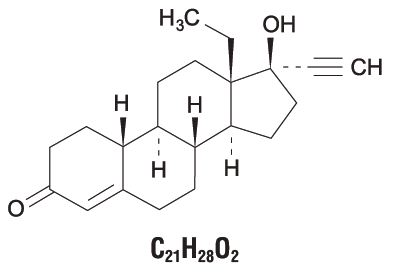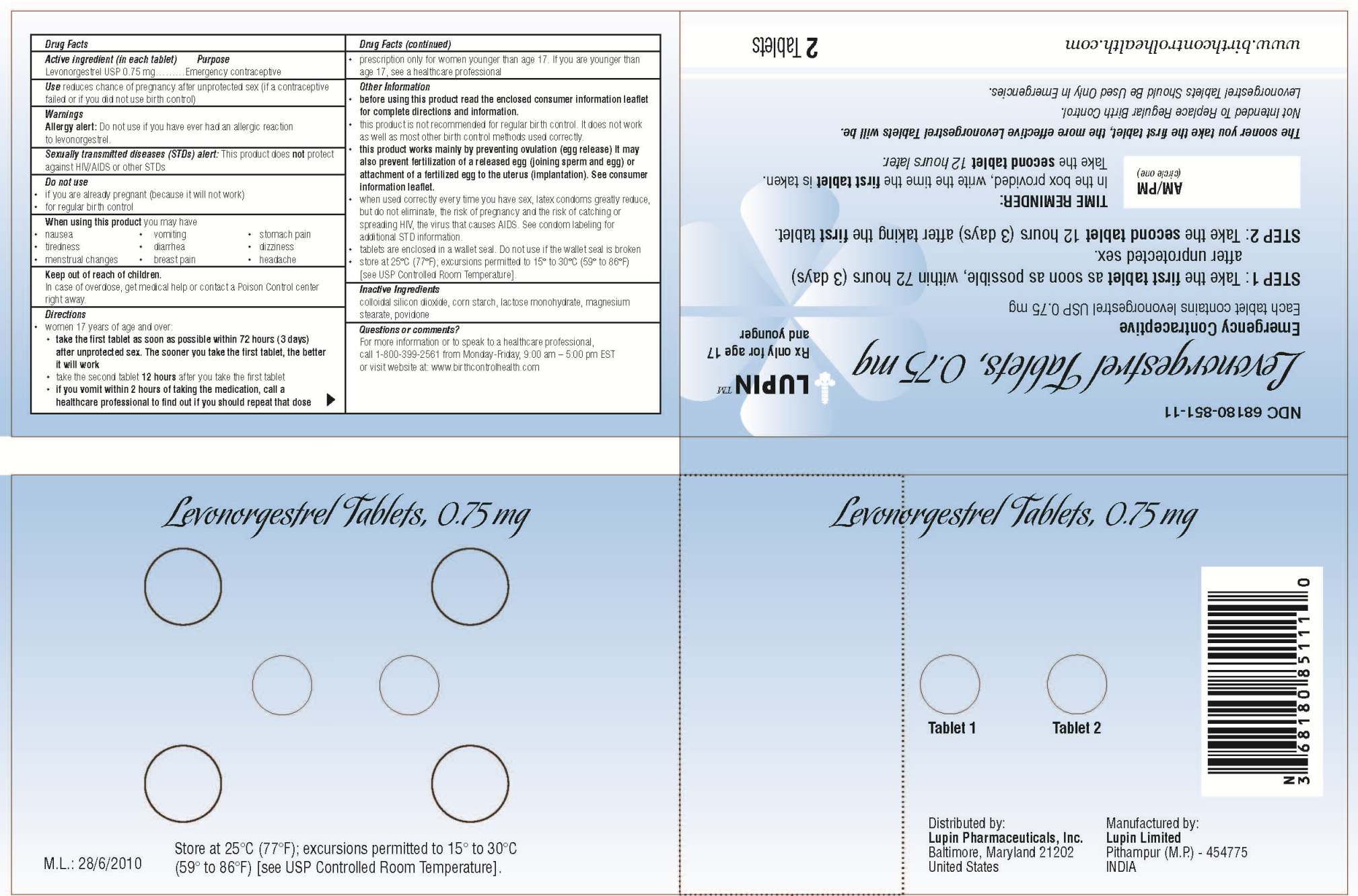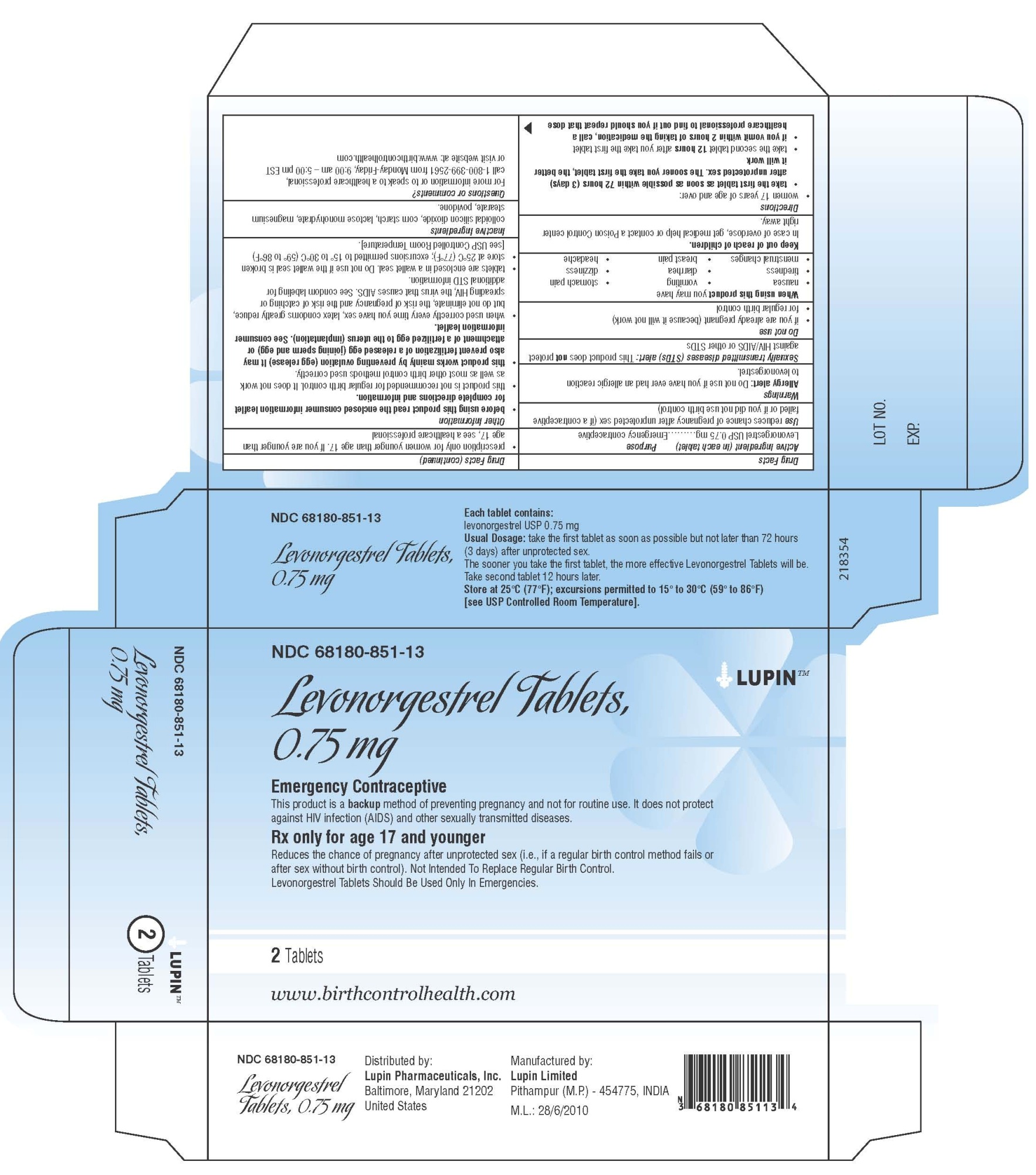 DRUG LABEL: Levonorgestrel
NDC: 68180-851 | Form: TABLET
Manufacturer: Lupin Pharmaceuticals, Inc.
Category: prescription | Type: HUMAN PRESCRIPTION DRUG LABEL
Date: 20190115

ACTIVE INGREDIENTS: LEVONORGESTREL 0.75 mg/1 1
INACTIVE INGREDIENTS: SILICON DIOXIDE; STARCH, CORN; POVIDONE; LACTOSE MONOHYDRATE; MAGNESIUM STEARATE

HIGHLIGHTS OF PRESCRIBING INFORMATION

These highlights do not include all the information needed to use LEVONORGESTREL TABLETS, 0.75 mg safely and effectively. See full prescribing information for LEVONORGESTREL TABLETS, 0.75 mg.
Levonorgestrel Tablets, 0.75 mg, for oral use
Initial U.S. Approval: 1982

1 INDICATIONS AND USAGE

Levonorgestrel tablets, 0.75 mg are progestin-only emergency contraceptive, indicated for prevention of pregnancy following unprotected intercourse or a known or suspected contraceptive failure. Levonorgestrel tablets, 0.75 mg are available only by prescription for women younger than age 17 years, and available over the counter for women 17 years and older. Levonorgestrel tablets, 0.75 mg are not intended for routine use as a contraceptive. (1)

2 DOSAGE AND ADMINISTRATION

The first tablet is taken orally as soon as possible within 72 hours after unprotected intercourse. The second tablet should be taken 12 hours after the first dose. Efficacy is better if levonorgestrel tablet, 0.75 mg is taken as soon as possible after unprotected intercourse. (2)

3 DOSAGE FORMS AND STRENGTHS

A total of two 0.75 mg tablets taken 12 hours apart as a single course of treatment. (3)

4 CONTRAINDICATIONS

Known or suspected pregnancy. (4)

5 WARNINGS AND PRECAUTIONS

- Ectopic Pregnancy: Women who become pregnant or complain of lower abdominal pain after taking levonorgestrel tablets, 0.75 mg should be evaluated for ectopic pregnancy. (5.1)
- Levonorgestrel tablets, 0.75 mg are not effective in terminating an existing pregnancy. (5.2)
- Effect on menses: Levonorgestrel tablets, 0.75 mg may alter the next expected menses. If menses is delayed beyond 1 week, pregnancy should be considered. (5.3)
- STI/HIV: Levonorgestrel tablets, 0.75 mg does not protect against STI/HIV. (5.4)

6 ADVERSE REACTIONS

The most common adverse reactions (≥10%) in the clinical trial included menstrual changes (26%), nausea (23%), abdominal pain (18%), fatigue (17%), headache (17%), dizziness (11%) and breast tenderness (11%). (6.1)

To report SUSPECTED ADVERSE REACTIONS, contact Lupin Pharmaceuticals Inc. at 1-800-399-2561 or FDA at 1-800-FDA-1088 or www.fda.gov/medwatch.

7 DRUG INTERACTIONS

Drugs or herbal products that induce certain enzymes, such as CYP3A4, may decrease the effectiveness of progestin-only pills. (7)

8 USE IN SPECIFIC POPULATIONS

- Nursing Mothers: Small amounts of progestin pass into the breast milk of nursing women taking progestin-only pills for long-term contraception, resulting in detectable steroid levels in infant plasma. (8.3)
- Levonorgestrel tablets, 0.75 mg are not intended for use in pediatric (premenarcheal) (8.4) or postmenopausal women (8.5).
- Clinical trials demonstrated a higher pregnancy rate in the Chinese population. (8.6)

FULL PRESCRIBING INFORMATION

1 INDICATIONS AND USAGE

Levonorgestrel tablets, 0.75 mg are progestin-only emergency contraceptive indicated for prevention of pregnancy following unprotected intercourse or a known or suspected contraceptive failure. To obtain optimal efficacy, the first tablet should be taken as soon as possible within 72 hours of intercourse. The second tablet should be taken 12 hours later.

Levonorgestrel tablets, 0.75 mg are available only by prescription for women younger than age 17 years, and available over the counter for women 17 years and older.

Levonorgestrel tablets, 0.75 mg are not indicated for routine use as a contraceptive.

2 DOSAGE AND ADMINISTRATION

Take one tablet of levonorgestrel tablet, 0.75 mg orally as soon as possible within 72 hours after unprotected intercourse or a known or suspected contraceptive failure. Efficacy is better if the tablet is taken as soon as possible after unprotected intercourse. The second tablet should be taken 12 hours after the first dose. Levonorgestrel tablets, 0.75 mg can be used at any time during the menstrual cycle.

If vomiting occurs within two hours of taking either dose of medication, consideration should be given to repeating the dose.

3 DOSAGE FORMS AND STRENGTHS

Each levonorgestrel tablet, 0.75 mg is supplied as a white to off white round biconvex tablets, debossed with ‘LU’ on one side and ‘S24’ on the other side.

4 CONTRAINDICATIONS

Levonorgestrel tablets, 0.75 mg are contraindicated for use in the case of known or suspected pregnancy.

5 WARNINGS AND PRECAUTIONS

5.1 Ectopic Pregnancy

Ectopic pregnancies account for approximately 2% of all reported pregnancies. Up to 10% of pregnancies reported in clinical studies of routine use of progestin-only contraceptives are ectopic.

A history of ectopic pregnancy is not a contraindication to use of this emergency contraceptive method. Healthcare providers, however, should consider the possibility of an ectopic pregnancy in women who become pregnant or complain of lower abdominal pain after taking levonorgestrel tablets, 0.75 mg. A follow-up physical or pelvic examination is recommended if there is any doubt concerning the general health or pregnancy status of any woman after taking levonorgestrel tablets, 0.75 mg.

5.2 Existing Pregnancy

Levonorgestrel tablets, 0.75 mg are not effective in terminating an existing pregnancy.

5.3 Effects on Menses

Some women may experience spotting a few days after taking levonorgestrel tablets, 0.75 mg. Menstrual bleeding patterns are often irregular among women using progestin-only oral contraceptives and women using levonorgestrel for postcoital and emergency contraception.

If there is a delay in the onset of expected menses beyond 1 week, consider the possibility of pregnancy.

5.4 STI/HIV

Levonorgestrel tablets, 0.75 mg do not protect against HIV infection (AIDS) or other sexually transmitted infections (STIs).

5.5 Physical Examination and Follow-up

A physical examination is not required prior to prescribing levonorgestrel tablets, 0.75 mg. A follow-up physical or pelvic examination is recommended if there is any doubt concerning the general health or pregnancy status of any woman after taking levonorgestrel tablets, 0.75 mg.

5.6 Fertility Following Discontinuation

A rapid return of fertility is likely following treatment with levonorgestrel tablets, 0.75 mg for emergency contraception; therefore, routine contraception should be continued or initiated as soon as possible following use of levonorgestrel tablets, 0.75 mg to ensure ongoing prevention of pregnancy.

6 ADVERSE REACTIONS

6.1 Clinical Trial Experience

Because clinical trials are conducted under widely varying conditions, adverse reaction rates observed in the clinical trials of a drug cannot be directly compared to rates in the clinical trials of another drug and may not reflect the rates observed in clinical practice.

A double-blind, controlled clinical trial in 1,955 evaluable women compared the efficacy and safety of levonorgestrel tablet, 0.75 mg (one 0.75 mg tablet of levonorgestrel taken within 72 hours of unprotected intercourse, and one tablet taken 12 hours later) to the Yuzpe regimen (two tablets each containing 0.25 mg levonorgestrel and 0.05 mg ethinyl estradiol, taken within 72 hours of intercourse, and two tablets taken 12 hours later).

The most common adverse events (>10%) in the clinical trial for women receiving levonorgestrel tablets, 0.75 mg included menstrual changes (26%), nausea (23%), abdominal pain (18%), fatigue (17%), headache (17%), dizziness (11%), and breast tenderness (11%). Table 1 lists those adverse events that were reported in ≥5% of levonorgestrel tablets, 0.75 mg users.

Table 1. Adverse Events in ≥ 5% of Women, by % Frequency
 | Levonorgestrel Tablets, 0.75 mg N = 977 (%)
Nausea | 23.1
Abdominal Pain | 17.6
Fatigue | 16.9
Headache | 16.8
Heavier Menstrual Bleeding | 13.8
Lighter Menstrual Bleeding | 12.5
Dizziness | 11.2
Breast Tenderness | 10.7
Vomiting | 5.6
Diarrhea | 5.0

6.2 Postmarketing Experience

The following adverse reactions have been identified during post-approval use of levonorgestrel tablets, 0.75 mg. Because these reactions are reported voluntarily from a population of uncertain size, it is not always possible to reliably estimate their frequency or establish a causal relationship to drug exposure.

Gastrointestinal Disorders

Abdominal Pain, Nausea, Vomiting

General Disorders and Administration Site Conditions

Fatigue

Nervous System Disorders

Dizziness, Headache

Reproductive System and Breast Disorders

Dysmenorrhea, Irregular Menstruation, Oligomenorrhea, Pelvic Pain

7 DRUG INTERACTIONS

Drugs or herbal products that induce enzymes, including CYP3A4, that metabolize progestins may decrease the plasma concentrations of progestins, and may decrease the effectiveness of progestin-only pills. Some drugs or herbal products that may decrease the effectiveness of progestin-only pills include:

- barbiturates (including primidone)
- bosentan
- carbamazepine
- felbamate
- griseofulvin
- oxcarbazepine
- phenytoin
- rifampin
- St. John's wort
- topiramate

Significant changes (increase or decrease) in the plasma levels of the progestin have been noted in some cases of co-administration with HIV protease inhibitors or with non-nucleoside reverse transcriptase inhibitors. Concomitant administration of efavirenz has been found to reduce plasma levels of levonorgestrel (AUC) by around 50%, which may reduce the effectiveness of levonorgestrel tablets, 0.75 mg.

Consult the labeling of all concurrently used drugs to obtain further information about interactions with progestin-only pills or the potential for enzyme alterations.

8 USE IN SPECIFIC POPULATIONS

8.1 Pregnancy

Many studies have found no harmful effects on fetal development associated with long-term use of contraceptive doses of oral progestins. The few studies of infant growth and development that have been conducted with progestin-only pills have not demonstrated significant adverse effects.

8.3 Nursing Mothers

In general, no adverse effects of progestin-only pills have been found on breastfeeding performance or on the health, growth or development of the infant. However, isolated post-marketing cases of decreased milk production have been reported. Small amounts of progestins pass into the breast milk of nursing mothers taking progestin-only pills for long-term contraception, resulting in detectable steroid levels in infant plasma.

8.4 Pediatric Use

Safety and efficacy of progestin-only pills for long-term contraception have been established in women of reproductive age. Safety and efficacy are expected to be the same for postpubertal adolescents under the age of 16 and for users 16 years and older. Use of levonorgestrel tablets, 0.75 mg emergency contraception before menarche is not indicated.

8.5 Geriatric Use

This product is not intended for use in postmenopausal women.

8.6 Race

No formal studies have evaluated the effect of race. However, clinical trials demonstrated a higher pregnancy rate in Chinese women with both levonorgestrel tablets, 0.75 mg and the Yuzpe regimen (another form of emergency contraception). The reason for this apparent increase in the pregnancy rate with emergency contraceptives in Chinese women is unknown.

8.7 Hepatic Impairment

No formal studies were conducted to evaluate the effect of hepatic disease on the disposition of levonorgestrel tablets, 0.75 mg.

8.8 Renal Impairment

No formal studies were conducted to evaluate the effect of renal disease on the disposition of levonorgestrel tablets, 0.75 mg.

9 DRUG ABUSE AND DEPENDENCE

Levonorgestrel is not a controlled substance. There is no information about dependence associated with the use of levonorgestrel tablets, 0.75 mg.

10 OVERDOSAGE

There are no data on overdosage of levonorgestrel tablets, 0.75 mg, although the common adverse event of nausea and associated vomiting may be anticipated.

11 DESCRIPTION

Each levonorgestrel tablets, 0.75 mg contains 0.75 mg of a single active steroid ingredient, levonorgestrel [18,19-Dinorpregn-4-en-20-yn-3-one-13-ethyl-17-hydroxy-, (17 α)-(-)-], a totally synthetic progestogen. The inactive ingredients present are colloidal silicon dioxide, corn starch, lactose monohydrate, magnesium stearate, and povidone.

Levonorgestrel has a molecular weight of 312.45, and the following structural and molecular formulas:

12 CLINICAL PHARMACOLOGY

12.1 Mechanism of Action

Emergency contraceptive pills are not effective if a woman is already pregnant. Levonorgestrel tablets, 0.75 mg are believed to act as an emergency contraceptive principally by preventing ovulation or fertilization (by altering tubal transport of sperm and/or ova). In addition, it may inhibit implantation (by altering the endometrium). It is not effective once the process of implantation has begun.

12.3 Pharmacokinetics

Absorption

No specific investigation of the absolute bioavailability of levonorgestrel in humans has been conducted. However, literature indicates that levonorgestrel is rapidly and completely absorbed after oral administration (bioavailability about 100%) and is not subject to first pass metabolism.

After a single dose of levonorgestrel (0.75 mg) administered to 16 women under fasting conditions, the maximum serum concentrations of levonorgestrel were 14.1 + 7.7 ng/mL (mean + SD) at an average of 1.6 + 0.7 hours.

 | Mean (± SD)
 | Cmax (ng/mL) | Tmax (h) | CL (L/h) | Vd (L) | t½ (h) | AUCinf (ng/mL.h)
Levonorgestrel | 14.1 (7.7) | 1.6 (0.7) | 7.7 (2.7) | 260.0 | 24.4 (5.3) | 123.1 (50.1)
Cmax = maximum concentration
Tmax = time to maximum concentration
CL = clearance
Vd = volume of distribution
t½ = elimination half life
AUCinf = area under the drug concentration curve from time 0 to infinity

Effect of Food: The effect of food on the rate and the extent of levonorgestrel absorption following single oral administration of levonorgestrel tablets, 0.75 mg have not been evaluated.

Distribution

The apparent volume of distribution of levonorgestrel is reported to be approximately 1.8 L/kg. It is about 97.5 to 99% protein-bound, principally to sex hormone binding globulin (SHBG) and, to a lesser extent, serum albumin.

Metabolism

Following absorption, levonorgestrel is conjugated at the 17β-OH position to form sulfate conjugates and, to a lesser extent, glucuronide conjugates in plasma. Significant amounts of conjugated and unconjugated 3α, 5β-tetrahydrolevonorgestrel are also present in plasma, along with much smaller amounts of 3α, 5α-tetrahydrolevonorgestrel and 16βhydroxylevonorgestrel. Levonorgestrel and its phase I metabolites are excreted primarily as glucuronide conjugates. Metabolic clearance rates may differ among individuals by several-fold, and this may account in part for the wide variation observed in levonorgestrel concentrations among users.

Excretion

About 45% of levonorgestrel and its metabolites are excreted in the urine and about 32% are excreted in feces, mostly as glucuronide conjugates.

Specific Populations

Pediatric

This product is not intended for use in the pediatric (pre-menarcheal) population, and pharmacokinetic data are not available for this population.

Geriatric

This product is not intended for use in postmenopausal women and pharmacokinetic data are not available for this population.

Race

No formal studies have evaluated the effect of race on pharmacokinetics of levonorgestrel tablets, 0.75 mg. However, clinical trials demonstrated a higher pregnancy rate in Chinese women with both levonorgestrel tablets, 0.75 mg and the Yuzpe regimen (another form of emergency contraception). The reason for this apparent increase in the pregnancy rate with emergency contraceptives in Chinese women is unknown [see USE IN SPECIFIC POPULATIONS (8.6)].

Hepatic Impairment

No formal studies were conducted to evaluate the effect of hepatic disease on the disposition of levonorgestrel tablets, 0.75 mg.

Renal Impairment

No formal studies were conducted to evaluate the effect of renal disease on the disposition of levonorgestrel tablets, 0.75 mg.

Drug-Drug Interactions

No formal drug-drug interaction studies were conducted with levonorgestrel tablets, 0.75 mg [see DRUG INTERACTIONS (7)].

13 NONCLINICAL TOXICOLOGY

13.1 Carcinogenesis, Mutagenesis, Impairment of Fertility

Carcinogenicity: There is no evidence of increased risk of cancer with short-term use of progestins. There was no increase in tumorgenicity following administration of levonorgestrel to rats for 2 years at approximately 5 μg/day, to dogs for 7 years at up to 0.125 mg/kg/day, or to rhesus monkeys for 10 years at up to 250 μg/kg/day. In another 7 year dog study, administration of levonorgestrel at 0.5 mg/kg/day did increase the number of mammary adenomas in treated dogs compared to controls. There were no malignancies.

Genotoxicity: Levonorgestrel was not found to be mutagenic or genotoxic in the Ames Assay, in vitro mammalian culture assays utilizing mouse lymphoma cells and Chinese hamster ovary cells, and in an in vivo micronucleus assay in mice.

Fertility: There are no irreversible effects on fertility following cessation of exposures to levonorgestrel or progestins in general.

14 CLINICAL STUDIES

A double-blind, randomized, multinational controlled clinical trial in 1,955 evaluable women (mean age 27) compared the efficacy and safety of levonorgestrel tablets, 0.75 mg (one 0.75 mg tablet of levonorgestrel taken within 72 hours of unprotected intercourse, and one tablet taken 12 hours later) to the Yuzpe regimen (two tablets each containing 0.25 mg levonorgestrel and 0.05 mg ethinyl estradiol, taken within 72 hours of intercourse, and two additional tablets taken 12 hours later). After a single act of intercourse occurring anytime during the menstrual cycle, the expected pregnancy rate of 8% (with no contraceptive use) was reduced to approximately 1% with levonorgestrel tablets, 0.75 mg.

Emergency contraceptives are not as effective as routine hormonal contraception since their failure rate, while low based on a single use, would accumulate over time with repeated use [see INDICATIONS AND USAGE (1)].

At the time of expected menses, approximately 74% of women using levonorgestrel tablets, 0.75 mg had vaginal bleeding similar to their normal menses, 14% bled more than usual, and 12% bled less than usual. The majority of women (87%) had their next menstrual period at the expected time or within +7 days, while 13% had a delay of more than 7 days beyond the anticipated onset of menses.

16 HOW SUPPLIED/STORAGE AND HANDLING

Levonorgestrel Tablets, 0.75 mg are white to off white round biconvex tablets, debossed with "LU" on one side and "S24" on the other side.

Levonorgestrel Tablets, 0.75 mg are available in a wallet containing 2 tablets (NDC 68180-851-11). Each wallet is packed in a carton (NDC 68180-851-13).

Store Levonorgestrel Tablets, 0.75 mg at 25°C (77°F); excursions permitted to 15° to 30°C (59° to 86°F). [see USP Controlled Room Temperature].

17 PATIENT COUNSELING INFORMATION

17.1 Information for Patients

- Take levonorgestrel tablet, 0.75 mg as soon as possible and not more than 72 hours after unprotected intercourse or a known or suspected contraceptive failure.
- If you vomit within two hours of taking either tablet, immediately contact your healthcare provider to discuss whether to take another tablet.
- Seek medical attention if you experience severe lower abdominal pain 3 to 5 weeks after taking levonorgestrel tablet, 0.75 mg, in order to be evaluated for an ectopic pregnancy.
- After taking levonorgestrel tablet, 0.75 mg, consider the possibility of pregnancy if your period is delayed more than one week beyond the date you expected your period.
- Do not use levonorgestrel tablet, 0.75 mg as routine contraception.
- Levonorgestrel tablets, 0.75 mg are not effective in terminating an existing pregnancy.
- Levonorgestrel tablet, 0.75 mg does not protect against HIV-infection (AIDS) and other sexually transmitted diseases/infections.
- For women younger than age 17 years, levonorgestrel tablets, 0.75 mg are available only by prescription.

Distributed by:

Lupin Pharmaceuticals, Inc.

Baltimore, Maryland 21202

United States

Manufactured by:

Lupin Limited

Pithampur (M.P.) - 454 775

INDIA

January 2018 ID#: 226728

PACKAGE LABEL.PRINCIPAL DISPLAY PANEL

Levonorgestrel Tablets, 0.75 mg

Rx only for age 17 and younger

NDC 68180-851-11

Wallet Label: 2 Tablets

Levonorgestrel Tablets, 0.75 mg

Rx only for age 17 and younger

NDC 68180-851-13

Carton Label: 2 Tablets